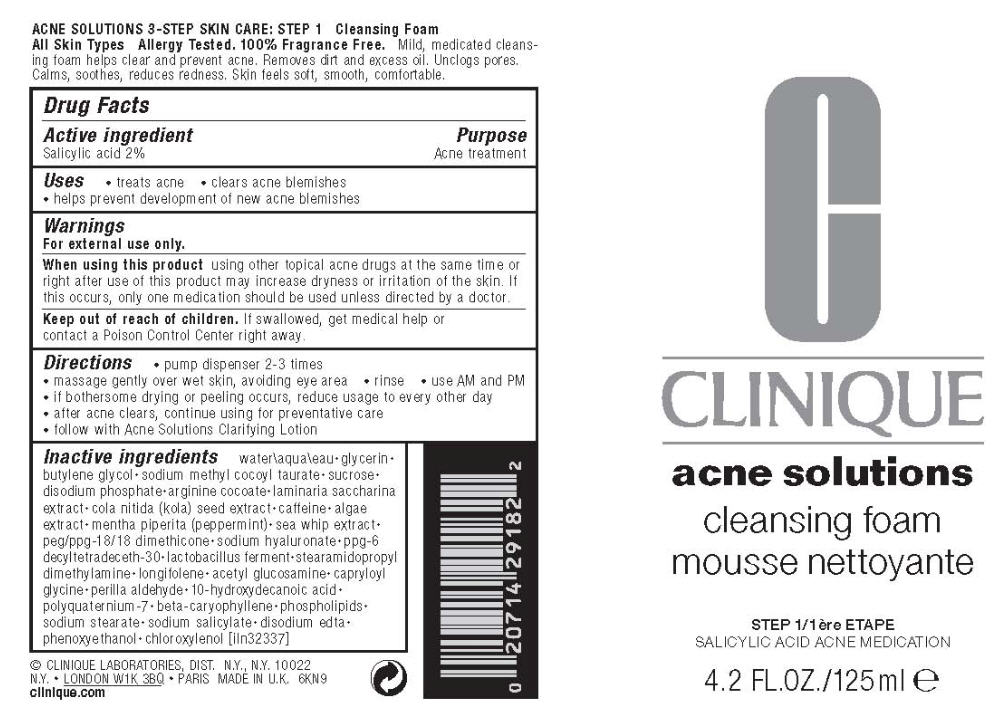 DRUG LABEL: ACNE SOLUTIONS 
NDC: 49527-992 | Form: LIQUID
Manufacturer: CLINIQUE  LABORATORIES INC
Category: otc | Type: HUMAN OTC DRUG LABEL
Date: 20110929

ACTIVE INGREDIENTS: salicylic acid 2 mL/100 mL
INACTIVE INGREDIENTS: water; glycerin; butylene glycol; sodium methyl cocoyl taurate; sucrose; saccharina latissima thallus; cola nut; caffeine; peppermint; pseudopterogorgia elisabethae; hyaluronate sodium; stearamidopropyl dimethylamine; N-acetylglucosamine; capryloyl glycine; perillaldehyde; 10-hydroxydecanoic acid; caryophyllene; sodium stearate; sodium salicylate; edetate disodium; phenoxyethanol; chloroxylenol

CLINIQUE
acne solutions

Drug Facts

Active ingredient

Salicylic acid 2%

Purpose

Acne treatment

Uses

- treats acne
- clears acne blemishes
- helps prevent development of new acne blemishes

Warnings

For external use only.

When using this product using other topical acne drugs at the same time or right after use of this product may increase dryness or irritation of the skin. If this occurs, only one medication should be used unless directed by a doctor.

Keep out of reach of children. If swallowed, get medical help or contact a Poison Control Center right away.

Directions

- pump dispenser 2-3 times
- massage gently over wet skin, avoiding eye area
- rinse
- use AM and PM
- if bothersome drying or peeling occurs, reduce usage to every other day
- after acne clears, continue using for preventative care
- follow with Acne Solutions Clarifying Lotion

Inactive ingredients

water, glycerin • butylene glycol • sodium methyl cocoyl taurate • sucrose • disodium phosphate • arginine cocoate • laminaria saccharina extract• cola nitida (kola) seed extract • caffeine • algae extract • mentha piperita (peppermint) • sea whip extract • peg/ppg-18/18 dimethicone • sodium hyaluronate • ppg-6 decyltetradeceth-30 • lactobacillus ferment • stearamidopropyl dimethylamine • longifolene • acetyl glucosamine • capryloyl glycine • perilla aldehyde • 10-hydroxydecanoic acid • polyquaternium-7 • beta-caryophyllene • phospholipids • sodium stearate • sodium salicylate • disodium edta • phenoxyethanol • chloroxylenol [iln32337]

© CLINIQUE LABORATORIES, DIST. N.Y., N.Y. 10022

PRINCIPAL DISPLAY PANEL - 125 ml Bottle Label

C
CLINIQUE
acne solutions

cleansing foam

STEP 1
SALICYLIC ACID ACNE MEDICATION

4.2 FL.OZ./125 ml e